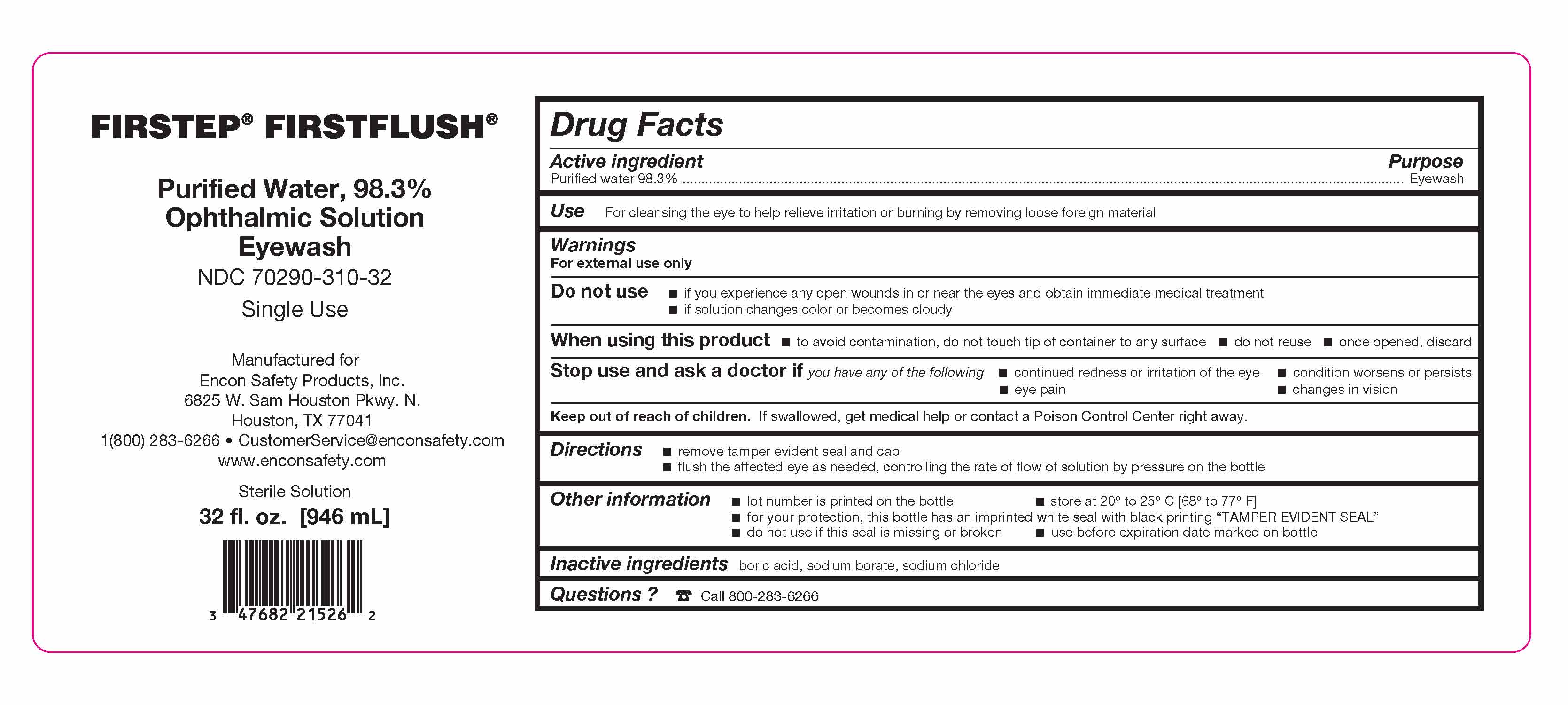 DRUG LABEL: Firstep Firstflush
NDC: 70290-310 | Form: SOLUTION
Manufacturer: Encon Safety Products, Inc.
Category: otc | Type: HUMAN OTC DRUG LABEL
Date: 20251209

ACTIVE INGREDIENTS: WATER 465 mL/473 mL
INACTIVE INGREDIENTS: BORIC ACID; SODIUM BORATE; SODIUM CHLORIDE

Encon Firstep Firstflush

Active ingredient

Purified water 98.3%

Purpose

Eyewash

Warnings

For external use only

Do not use

- if you experience any open wounds in or near the eyes and obtain immediate medical treatment
- if solution changes color or becomes cloudy

When using this product

- to avoid contamination, do not touch tip of container to any surface
- do not reuse
- once opened, discard

Use

For cleansing the eye to help relieve irritation or burning by removing loose foreign material

Stop use and ask a doctor if you have any of the following

- continued redness or irritation of the eye
- condition worsens or persists
- eye pain
- changes in vision

Keep out of reach of children

If swallowed, get medical help or contact a Poison Control Center right away.

Directions

- remove tamper evident seal and cap
- flush the affected eye as needed, controlling the rate of flow of solution by pressure on the bottle

Other information

- lot number is printed on the bottle
- store at 20° to 25° C [68° to 77° F]
- for your protection, this bottle has an imprinted white seal with black printing “TAMPER EVIDENT SEAL”
- do not use if this seal is missing or broken
- use before expiration date marked on bottle

Inactive ingredients

boric acid, sodium borate, sodium chloride

Questions?

☎ Call 973-227-1830 9 a.m. to 5 p.m. EST Mon-Fri

Dosage and Administration

- remove tamper evident seal and cap
- flush the affected eye as needed, controlling the rate of flow of solution by pressure on the bottle

Dosage and Administration

- remove tamper evident seal and cap
- flush the affected eye as needed, controlling the rate of flow of solution by pressure on the bottle

Warnings

For external use only